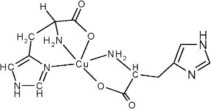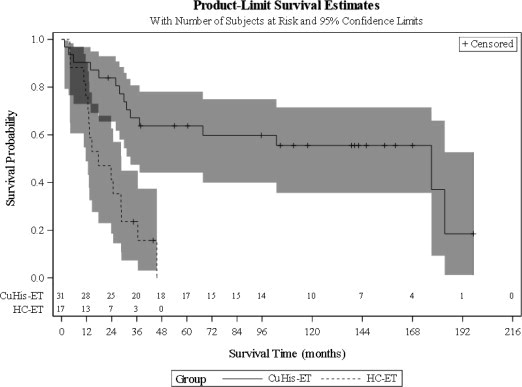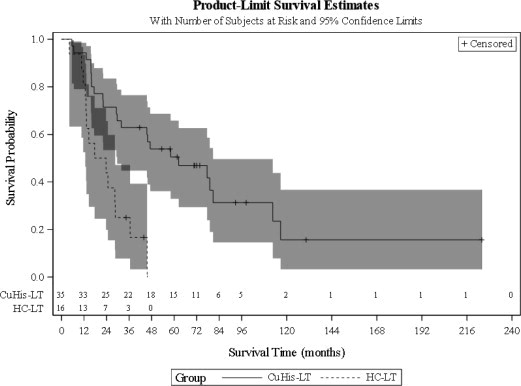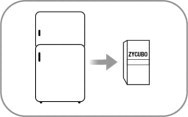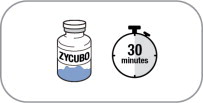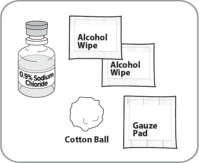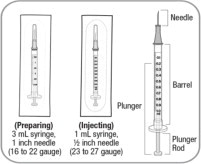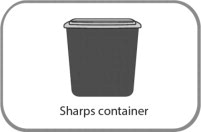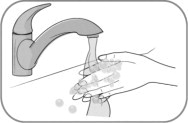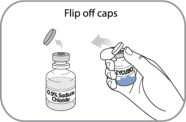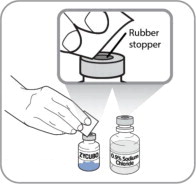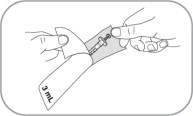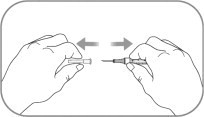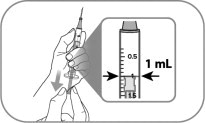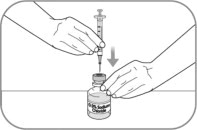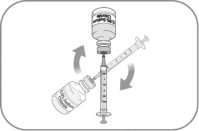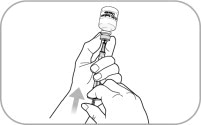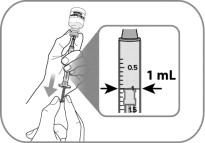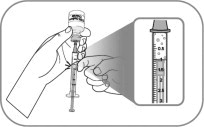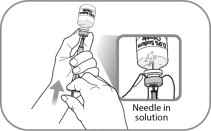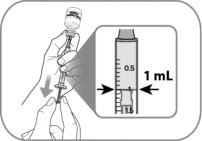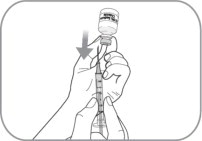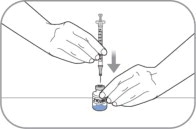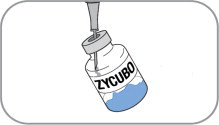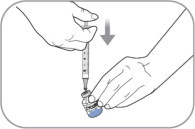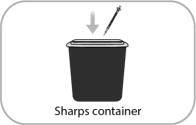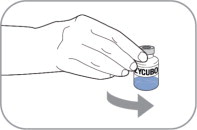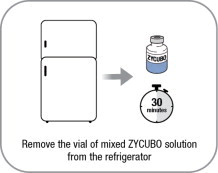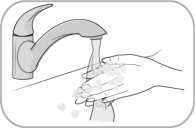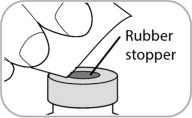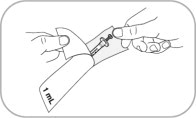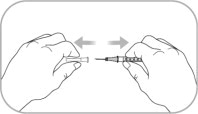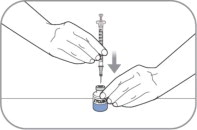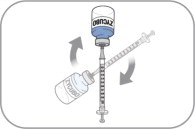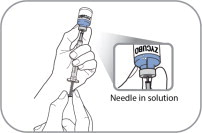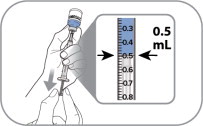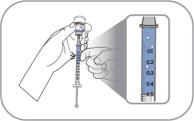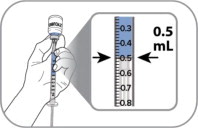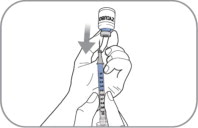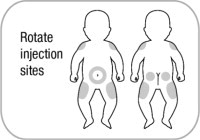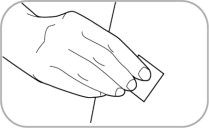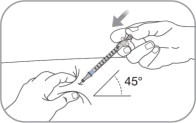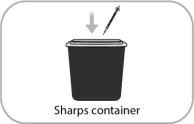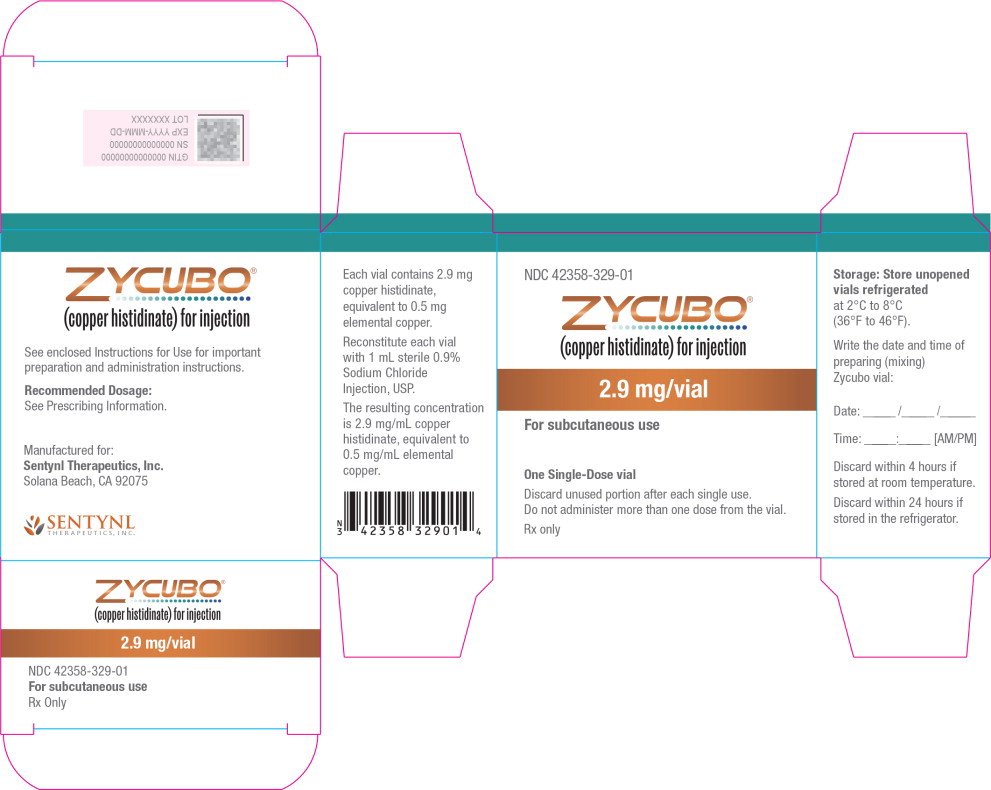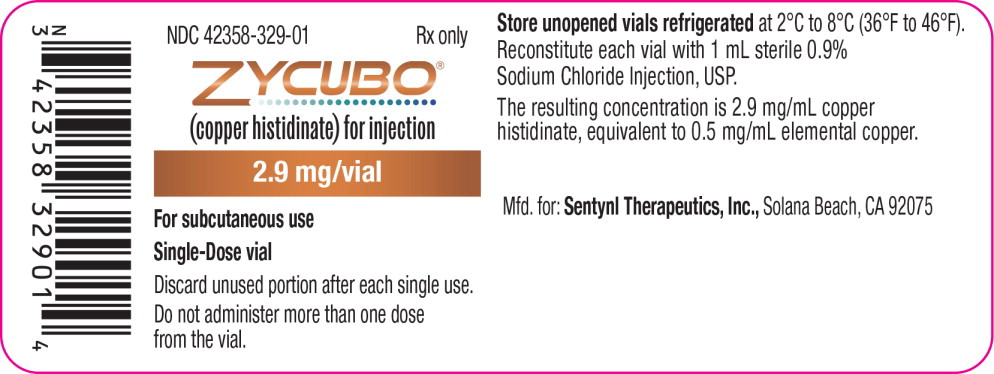 DRUG LABEL: Zycubo
NDC: 42358-329 | Form: INJECTION, POWDER, LYOPHILIZED, FOR SOLUTION
Manufacturer: Sentynl Therapeutics, Inc.
Category: prescription | Type: HUMAN PRESCRIPTION DRUG LABEL
Date: 20260112

ACTIVE INGREDIENTS: copper histidinate 2.9 mg/1 1

HIGHLIGHTS OF PRESCRIBING INFORMATION

These highlights do not include all the information needed to use ZYCUBO safely and effectively. See full prescribing information for ZYCUBO.
ZYCUBO® (copper histidinate) for injection, for subcutaneous use
Initial U.S. Approval: 2026

1 INDICATIONS AND USAGE

ZYCUBO is a copper replacement product indicated for the treatment of Menkes disease in pediatric patients. (1)

Limitations of Use

ZYCUBO is not indicated for the treatment of Occipital Horn Syndrome. (1)

2 DOSAGE AND ADMINISTRATION

- Before initiating ZYCUBO, obtain baseline serum copper and ceruloplasmin levels, serum electrolytes, kidney and liver function, and complete blood count. (2.1)
- The recommended dosage of ZYCUBO in pediatric patients:
  - Less than 1 year of age is 1.45 mg twice daily (8-12 hours between injections). (2.2)
  - 1 year of age to less than 17 years of age is 1.45 mg once daily. (2.2)
- Monitor serum copper and ceruloplasmin levels, serum electrolytes, kidney and liver function, and complete blood count (CBC). (2.3)
- Reconstitute ZYCUBO and administer subcutaneously. (2.4, 2.6)
- See Full Prescribing Information for additional preparation, storage, and administration instructions. (2.4, 2.5, 2.6)

3 DOSAGE FORMS AND STRENGTHS

For Injection: 2.9 mg of copper histidinate (equivalent to 0.5 mg elemental copper) as a lyophilized powder or cake in a single-dose vial for reconstitution. (3)

4 CONTRAINDICATIONS

- None (4)

5 WARNINGS AND PRECAUTIONS

Copper Accumulation and Risk of Toxicity: Exogenous administration of copper with ZYCUBO may lead to further copper accumulation and has the potential to result in drug-induced kidney injury, liver dysfunction, and hematological abnormalities. Monitor patients during ZYCUBO treatment. Adjust dosage if necessary. (2.2, 5.1, 6.1)

6 ADVERSE REACTIONS

Most common adverse reactions (incidence ≥7%) were pneumonia, viral infection, respiratory failure, seizure, bacterial infection, hemorrhage, hypotension, vomiting, tachycardia, pyrexia, volume depletion, fracture, dyspnea, transaminases elevation, diarrhea, fungal infection, anemia, and local administration reaction. (6.1)

To report SUSPECTED ADVERSE REACTIONS, contact Sentynl Therapeutics, Inc. at 1-888-507-5206 or FDA at 1-800-FDA-1088 or www.fda.gov/medwatch.

FULL PRESCRIBING INFORMATION

1 INDICATIONS AND USAGE

ZYCUBO is indicated for the treatment of Menkes disease in pediatric patients.

Limitations of Use

ZYCUBO is not indicated for the treatment of Occipital Horn Syndrome.

2 DOSAGE AND ADMINISTRATION

2.1 Recommended Testing Before Initiating ZYCUBO

Before initiating ZYCUBO, obtain baseline serum copper and ceruloplasmin levels, serum electrolytes, kidney and liver function, and complete blood count (CBC) [see Warnings and Precautions (5.1)].

2.2 Recommended Dosage and Administration

The recommended dosage of ZYCUBO in pediatric patients:

- Less than 1 year of age is 1.45 mg administered subcutaneously twice daily (8-12 hours between injections).
- 1 year of age to less than 17 years of age is 1.45 mg administered subcutaneously once daily.

2.3 Dosage and Administration Modifications and Monitoring

Monitor serum copper and ceruloplasmin levels, serum electrolytes, kidney and liver function, and complete blood count (CBC) every 6 weeks for the first 6 months, then every 3 months for 18 months, and then every 6 months thereafter during ZYCUBO treatment. If laboratory abnormalities are detected, consider reducing the frequency of ZYCUBO administration or temporarily withholding or permanently discontinuing ZYCUBO. Return to increased frequency of laboratory evaluation when resuming a dosage as clinically indicated [see Warnings and Precautions (5.1)].

2.4 Preparation Instructions

Preparation

- Use aseptic technique during preparation. Reconstitute ZYCUBO using a sterile disposable 3 mL syringe and 1 inch needle (between 16 to 22 gauge) (see Instructions for Use).
- Remove 1 ZYCUBO vial from the refrigerator and set aside for approximately 30 minutes to allow the vial to come to room temperature [20°C to 25°C (68°F to 77°F)] before use.
- Reconstitute ZYCUBO by tilting the vial and slowly injecting 1 mL of 0.9% Sodium Chloride Injection, USP down the inside wall of the vial.
- Gently swirl the vial continuously until the powder is completely dissolved. Do not shake the vial. Each vial will yield a concentration of 2.9 mg/mL.
- Visually inspect the reconstituted solution in the vial for particulate matter and discoloration. The solution should be blue. Discard if particles are present or the solution is discolored (not blue) or cloudy.
- Do not mix with other medications.

2.5 Storage of Reconstituted Solution

If the reconstituted ZYCUBO vial is not used immediately, store the vial refrigerated at 2°C to 8°C (36° to 46°F) for up to 24 hours or at controlled room temperature at 20°C to 25°C (68°F to 77°F) for up to 4 hours.

Discard the reconstituted ZYCUBO vial if not used within 24 hours of refrigeration or within 4 hours at room temperature.

2.6 Administration Instructions

A caregiver may administer ZYCUBO to patients after proper training in subcutaneous injection technique if a healthcare provider determines that it is appropriate (see Instructions for Use). Administer ZYCUBO using a sterile disposable 1 mL syringe and 1/2 inch injection needle (between 23 to 27 gauge).

Slowly withdraw 0.5 mL of reconstituted ZYCUBO solution from the vial and inject subcutaneously.

Administer ZYCUBO by subcutaneous injection at separate sites in the abdominal area (2 inches from the navel), buttocks, and the outer lateral aspect of the upper arm or thigh. Rotate injection sites with each injection to reduce the risk of lipodystrophy. Do not give injections into areas where the skin is scarred, tender, bruised, red, or hard.

Discard unused portion after each single use. Do not administer more than one dose from the vial.

2.7 Missed Dose

If a ZYCUBO dose is missed, administer the missed dose as soon as possible. Administer the next scheduled dose at least 6 hours after the administration of the missed dose.

3 DOSAGE FORMS AND STRENGTHS

For Injection: 2.9 mg of copper histidinate (equivalent to 0.5 mg elemental copper) as a blue lyophilized powder or cake in a single-dose vial for reconstitution.

4 CONTRAINDICATIONS

None.

5 WARNINGS AND PRECAUTIONS

5.1 Copper Accumulation and Risk of Toxicity

Impaired copper transport in patients with Menkes disease can lead to copper accumulation and organ impairment in the kidneys, liver, and hematopoietic system. Treatment with ZYCUBO may lead to further copper accumulation and related toxicity, especially in the first two years of life given renal and hepatic immaturity.

Obtain baseline serum copper and ceruloplasmin levels, serum electrolytes, kidney and liver function, and complete blood count (CBC). After initiating ZYCUBO, monitor laboratory values every 6 weeks for the first 6 months, then every 3 months for 18 months, and then every 6 months thereafter during ZYCUBO treatment. If laboratory abnormalities are detected, consider reducing the frequency of ZYCUBO administration or temporarily withholding or permanently discontinuing ZYCUBO. Return to increased frequency of laboratory monitoring when resuming a dosage as clinically indicated.

Drug-Induced Kidney Injury

Copper accumulation with ZYCUBO use has the potential to result in renal tubular toxicity in patients with Menkes disease. Routinely monitor patients starting or re-starting ZYCUBO for signs and symptoms of renal tubular toxicity. New-onset or worsening non-anion gap metabolic acidosis may be a sign of drug-related renal tubular acidosis. Increased urinary beta-2 microglobulin and/or new-onset hypophosphatemia, hyponatremia, or hypokalemia may be signs of drug-related proximal renal tubular toxicity. Provide supportive care with electrolyte repletion and supplementation as clinically indicated.

Copper accumulation with ZYCUBO use has the potential to result in glomerular injury, leading to decreased kidney function or new-onset proteinuria.

Liver Dysfunction

Copper accumulation with ZYCUBO can result in liver dysfunction. Elevations of liver transaminases have been reported in patients taking ZYCUBO for Menkes disease [see Adverse Reactions (6.1)]. Single cell necrosis, inflammation, and fibrosis, along with increased liver transaminases and bilirubin were observed in studies conducted over 13-weeks in juvenile rats with normal baseline copper levels [see Use in Specific Populations (8.4)].

Hematological Abnormalities

Copper accumulation with ZYCUBO can result in spleen and bone marrow dysfunction as well as interference with iron metabolism. Anemia has been reported in patients taking ZYCUBO for Menkes disease [see Adverse Reactions (6.1)]. Increased cellularity and pigmented macrophages in the spleen and increased hematological values were observed in studies conducted over 13-weeks in normal juvenile rats [see Use in Specific Populations (8.4)].

6 ADVERSE REACTIONS

The following clinically significant adverse reactions are described elsewhere in the labeling:

- Copper Accumulation and Risk of Toxicity: Drug-Induced Kidney Injury, Liver Dysfunction, Hematological Abnormalities [see Warnings and Precautions (5.1)]

6.1 Clinical Trials Experience

Because clinical trials are conducted under widely varying conditions, adverse reaction rates observed in the clinical trials of a drug cannot be directly compared to rates in the clinical trials of another drug and may not reflect the rates observed in practice.

The pooled safety analysis from 2 open-label, single-arm clinical trials included a total of 129 ZYCUBO-treated patients with an age range from 0 to 48 months. Patients less than 1 year of age received ZYCUBO 1.45 mg twice daily, and patients 1 year of age and older received ZYCUBO 1.45 mg once daily. The median exposure duration was 24 months (range: 1 to 39 months) [see Clinical Studies (14)].

Serious Adverse Reactions

Serious adverse reactions reported in ≥5% of ZYCUBO-treated pediatric patients with Menkes disease were pneumonia, dehydration, seizure, respiratory distress, respiratory syncytial virus infection, cardiopulmonary failure, upper respiratory tract infection, respiratory failure, and vomiting.

Common Adverse Reactions

Table 1 lists the most common adverse reactions that occurred in ≥7% of patients in the pooled safety analysis during an observation period ranging from 1 to 39 months.

Table 1. Adverse Reactions Occurring in ≥7% Patients with Menkes Disease (Trial 1 and Trial 2)
Adverse Reactions | Menkes Disease (N = 129) N (%)
Pneumonia | 38 (30)
Viral infection | 35 (27)
Respiratory failure^1 | 30 (23)
Cardiopulmonary failure | 11 (9)
Seizure | 29 (23)
Bacterial infection | 26 (20)
Renal and urinary tract infection^2 | 12 (9)
Hemorrhage | 23 (18)
Hypotension | 20 (16)
Vomiting | 19 (15)
Tachycardia | 16 (12)
Pyrexia | 16 (12)
Volume depletion | 16 (12)
Fracture | 16 (12)
Dyspnea | 16 (12)
Transaminases elevation | 13 (10)
Diarrhea | 13 (10)
Fungal infection | 12 (9)
Anemia | 11 (9)
Local administration reaction | 9 (7)
^1Respiratory failure consists of multiple similar terms including cardiopulmonary failure.
^2Bacterial infection consists of multiple similar terms including renal and urinary tract infection.

8 USE IN SPECIFIC POPULATIONS

8.1 Pregnancy

Risk Summary

There are no available data on ZYCUBO use during pregnancy to evaluate for a drug-associated risk of major birth defects, miscarriage, or other adverse maternal or fetal outcomes. Animal reproduction studies have not been conducted with ZYCUBO.

The background risk of major birth defects and miscarriage for the indicated population is unknown. All pregnancies have a background risk of birth defects, loss, or other adverse outcomes. In the U.S. general population, the estimated background risk of major birth defects and miscarriage in clinically recognized pregnancies is 2%-4% and 15%-20%, respectively.

8.2 Lactation

Risk Summary

There are no data on the presence of copper histidinate and its metabolites in either human or animal milk, the effects on the breastfed infant, or the effects on milk production. The developmental and health benefits of breastfeeding should be considered along with the mother's clinical need for ZYCUBO and any potential adverse effects on the breastfed infant from ZYCUBO or from the underlying maternal condition.

8.4 Pediatric Use

The safety and effectiveness of ZYCUBO for the treatment of Menkes disease have been established in pediatric patients, and the information on this use is discussed throughout the labeling.

Juvenile Animal Toxicity Data

Juvenile rats with normal baseline copper levels were administered copper histidinate from postnatal day (PND) 10 (the equivalent of a human newborn) to PND 100 (the equivalent of a human adult) subcutaneously twice daily for 13 weeks at 1, 2, and 5 mg/kg. Histopathological findings were observed in the kidney (tubular necrosis, eosinophilic globules), liver (single cell necrosis, inflammation, fibrosis), and spleen (increased cellularity and pigmented macrophages), in addition to increased liver transaminases (ALT, AST) and bilirubin, and decreased red blood cells, hemoglobin and hematocrit at 5 mg/kg (10-fold the human plasma concentration at the recommended dose of ZYCUBO (based on Cmax)). Changes in liver (necrosis, inflammation, ALT, AST) and kidney (eosinophilic globules) were also noted as low as 1 mg/kg (equivalent to human plasma concentration at the recommended dose of ZYCUBO (based on Cmax)). A no-observed-adverse-effect-level (NOAEL) in juvenile rats could not be determined. Proportional increases in copper and ceruloplasmin levels occurred with increasing dose levels.

8.5 Geriatric Use

Menkes disease is a disease of pediatric patients. Clinical trials of ZYCUBO did not include patients 65 years of age and older.

11 DESCRIPTION

ZYCUBO (copper histidinate) for injection is a copper replacement product. The chemical name is copper, (L-histidinato-ϰN,ϰN3,ϰO)(L-histidinato-ϰN,ϰO)-, (SP-5-14-C)-. The molecular formula is C12H16CuN6O4, and the molecular weight is 371.84 g/mol. Copper histidinate is soluble in water.

The chemical structure is:

ZYCUBO is a sterile, preservative-free, blue lyophilized powder or cake for subcutaneous injection after reconstitution with 1 mL sterile 0.9% Sodium Chloride Injection, USP. Each single-dose vial contains 2.9 mg of copper histidinate (equivalent to 0.5 mg elemental copper). The resultant solution has a concentration of 2.9 mg/mL and a pH of 7.4.

12 CLINICAL PHARMACOLOGY

12.1 Mechanism of Action

Menkes disease is an X-linked recessive disorder caused by pathogenic variants in the copper transport ATPase encoded by ATP7A. Patients with Menkes disease have impaired absorption of copper from their diet, impaired transport of copper across the blood-brain barrier, and dysregulation of many copper-dependent enzymes. ZYCUBO is a bioavailable copper replacement therapy that is administered as a subcutaneous injection to bypass the impaired gastrointestinal absorption observed in patients with Menkes disease.

12.2 Pharmacodynamics

Patients with Menkes disease have low serum concentrations of copper and ceruloplasmin. Treatment with ZYCUBO increases serum copper and ceruloplasmin concentrations in patients with Menkes disease.

The exposure-response relationship and time course of pharmacodynamic response for the safety and effectiveness of ZYCUBO have not been fully characterized.

12.3 Pharmacokinetics

The geometric mean (CV%) maximum serum concentration (Cmax) of copper histidinate was 67 (36%) ng/mL, the geometric mean (CV%) area under the concentration-time curve from time 0 to 24 hours (AUC0-24hr) was 186 (21%) ng•hr/mL, and the geometric mean (CV%) area under the concentration-time curve from time 0 to infinity (AUC0-inf) was 296 (15%) ng•hr/mL following a single subcutaneous dose of 3 mg copper histidinate (approximately twice the approved recommended dose for Menkes disease patients 1 year old or older) in healthy adult subjects.

At the recommended dosage, the mean (SD) serum copper concentration increased from a baseline concentration of 30 (25) mcg/dL to 114 (38) mcg/dL at 12 months, and gradually decreased over the 36-month treatment period, with a mean (SD) serum copper concentration of 63 (31) mcg/dL at 36 months. The mean (SD) serum ceruloplasmin concentration was 12 (12) mg/dL at baseline, 33 (11) mg/dL at 12 months, and 20 (8) mg/dL at 36 months [see Clinical Studies (14)].

Absorption

The absolute bioavailability of copper histidinate following subcutaneous injection has not been determined. The median time to reach maximum serum concentrations of copper histidinate (Tmax) was 0.75 hours following a single subcutaneous dose of 3 mg copper histidinate (approximately twice the approved recommended dose for Menkes disease patients 1 year old or older) in healthy adult subjects.

Distribution

The mean (SD) apparent volume of distribution (Vz/F) of copper histidinate during the terminal elimination phase was 1034 (588) L following a single subcutaneous dose of 3 mg copper histidinate (approximately twice the approved recommended dose for Menkes disease patients 1 year old or older) in healthy adult subjects.

Serum copper histidinate concentration-time profiles exhibited an initial decrease followed by a terminal elimination phase, consistent with the release of copper from the copper histidinate complex to the carrier proteins ceruloplasmin and albumin, followed by incorporation of copper histidinate and histidine into the endogenous pools of copper histidinate and histidine, respectively.

No binding of copper histidinate to human plasma proteins in vitro has been observed.

Elimination

The mean (SD) serum clearance (CL/F) of copper histidinate was 10.3 (1.6) L/hr, and the mean terminal half-life was 75 hours following a single subcutaneous dose of 3 mg copper histidinate (approximately twice the approved recommended dose for Menkes disease patients 1 year old or older) in healthy adult subjects.

Metabolism

The metabolism of copper histidinate has not been well characterized.

Excretion

Elimination of elemental copper is through biliary excretion.

Drug Interaction Studies

In vitro Studies: Copper histidinate is a weak inhibitor of CYP1A2, CYP2B6, CYP2C9, CYP2C19, and CYP2D6 (IC50 >100 μM). Copper histidinate is not an inducer of CYP1A2, CYP2B6, or CYP3A.

Transporter Systems: Copper histidinate is not a substrate of BCRP, P-gp, MATE1, MATE2-K, OAT1, OAT3, OATP1B1, OAT1B3, or OCT2. Copper histidinate is an inhibitor of BSEP and MATE1. Copper histidinate is a weak inhibitor of BCRP, MATE2K, OCT1, and OCT2. Copper histidinate is not an inhibitor of P-gp, OAT1, OAT3, OATP1B1, or OATP1B3.

13 NONCLINICAL TOXICOLOGY

13.1 Carcinogenesis, Mutagenesis, Impairment of Fertility

Carcinogenesis

Animal studies to evaluate the carcinogenic potential of copper histidinate have not been conducted with ZYCUBO.

Mutagenesis

ZYCUBO was not mutagenic or clastogenic in a standard battery of genotoxicity tests [bacterial mutagenicity (Ames), micronucleus assay in TK6 cells (in vitro), and rat bone marrow micronucleus assay (in vivo)].

Impairment of Fertility

Animal studies to evaluate effects of copper histidinate on fertility and early embryonic development have not been conducted with ZYCUBO.

14 CLINICAL STUDIES

The efficacy of ZYCUBO was evaluated in pediatric patients with Menkes disease (age at treatment initiation ranges 0.1 to 31.4 months) receiving 3 years of copper histidinate treatment in two open-label, single-arm clinical trials (Trial 1, NCT00001262 and Trial 2, NCT00811785). Data from ZYCUBO-treated patients in these two trials were compared to data from an untreated contemporaneous external control cohort as collected under a protocol amendment of Trial 2. In both trials, pediatric patients:

- Less than 1 year of age received 1.45 mg of ZYCUBO administered subcutaneously twice daily until 1 year of age.
- Equal to or greater than 1 year of age received 1.45 mg of ZYCUBO subcutaneously once daily for up to 3 years.

Overall survival was evaluated in a subset of the pooled population from Trial 1 and Trial 2, referred to as the pooled efficacy population. This efficacy population included only patients with Menkes disease who carried a severe pathogenic variant of the ATP7A gene (duplication/deletion, nonsense, or a canonical splice junction variant) and were born after 1999. There were 83 pediatric patients (66 ZYCUBO; 17 external control) in this pooled efficacy population: 21 patients (21 ZYCUBO) from Trial 1 and 62 patients (45 ZYCUBO; 17 external control) from Trial 2.

Patients in the pooled efficacy population were assigned to 1 of 4 cohorts as described in Table 2.

Table 2. Patient Cohorts in the Pooled Efficacy Population
 | Treated Cohorts |  | Untreated Cohorts
 | ZYCUBO- Early Treatment (ZYCUBO-ET) n=31 | ZYCUBO- Late Treatment (ZYCUBO-LT) n=35 | External Control-Early Treatment (EC-ET) n=17 | External Control-Late Treatment (EC-LT) n=16
Eligibility | Started ZYCUBO treatment within 4 weeks of birth [1] | Started ZYCUBO treatment after 4 weeks of birth [2] | - No prior ZYCUBO or copper treatment - Asymptomatic for significant neurological signs and symptoms approximately 4 weeks after birth - Survived at least 4 weeks after diagnosis | - Subset of the EC-ET cohort - Diagnosed with Menkes disease after 4 weeks of birth - Survived at least 2 weeks after diagnosis
Age at diagnosis (months) | 0.1 (-4.5 – 1.9) | 4.8 (0.4 – 29.4) | 4.7 (2.1 – 22.2) | 5.6 (2.1 – 22.2)
Age at treatment initiation (months) | 0.4 (0.1 – 1.9) | 7.1 (1.3 – 31.4) | NA | NA
Treatment duration (months) | 34.1 (1.1 – 36) | 20 (1.3 – 36) | NA | NA
All values are in median (range)
^1 Within 4 weeks of birth or within 4 weeks of birth corrected for prematurity (i.e., < 40 weeks' gestation)
^2 After 4 weeks of birth or after 4 weeks of birth corrected for prematurity (i.e., < 40 weeks' gestation)

In the 4 cohorts, 81 patients were male (98%) except for 2 female (2%) patients in ZYCUBO-LT. The pooled efficacy population included patients with the following race and ethnicity: 52 White (63%), 11 Hispanic (13%), 8 Black or African American (10%), 6 Unknown (7%), 4 Other (5%), and 2 Asian or Pacific Islander (2%). The majority of patients in all 4 cohorts were born prematurely: ZYCUBO-ET = 77%, ZYCUBO-LT = 66%, EC-ET = 82%, and EC-LT = 81%.

Efficacy Results

Primary Efficacy Results (Overall Survival) in the ZYCUBO-ET and EC-ET Cohorts

The primary efficacy analysis compared the overall survival in patients in the ZYCUBO-ET and EC-ET cohorts. Patients in the ZYCUBO-ET cohort (patients treated with ZYCUBO) had a significant improvement in overall survival compared to patients in the EC-ET cohort, with a 78% reduction in the risk of death (Table 3 and Figure 1).

In the ZYCUBO-ET cohort, 15 (48%) patients survived >6 years, including 7 (23%) patients who survived >12 years. In the EC-ET cohort, no patients survived >6 years.

Table 3. Primary Efficacy Results: Overall Survival in ZYCUBO Early Treatment and External Control Early Treatment Cohorts with Menkes Disease
 | ZYCUBO-Early Treatment (n=31) | External Control-Early Treatment (n=17)
Number (%) of Patients Alive | 16 (52%) | 2 (12%)
Median survival time (months) (95% CI) | 177.1 (33, NE) | 17.6 (11.5, 28.6)
Hazard Ratio (95% CI) | 0.22 (0.10, 0.49)
CI=Confidence Interval; NE=Not estimable
Note: If death dates were unknown, patients were censored at the last known date alive.

Figure 1. Kaplan-Meier Overall Survival Curve for the ZYCUBO Early Treatment and External Control Early Treatment Cohorts with Menkes Disease

CuHis=copper histidinate; ET=early treatment; EC=external control

Secondary Efficacy Results (Overall Survival) in the ZYCUBO-LT and EC-LT Cohorts

The secondary efficacy analysis compared the overall survival in patients in the ZYCUBO-LT cohort with patients in the EC-LT cohort. Patients in the ZYCUBO-LT cohort (patients treated with ZYCUBO) had a significant improvement in overall survival compared to patients in the EC-LT cohort, with a 73% reduction in the risk of death (Table 4 and Figure 2).

Table 4. Secondary Efficacy Results: Overall Survival in ZYCUBO Late Treatment and External Control Late Treatment Cohorts with Menkes Disease
 | ZYCUBO Late-Treatment (LT) (n=35) | External Control-Late Treatment (EC-LT) (n=16)
Number of Patients Alive (%) | 12 (34%) | 2 (12%)
Median survival time (months) (95% CI) | 62.4 (29.6, 80.7) | 20.7 (12.6, 28.6)
Hazard Ratio (95% CI) | 0.27 (0.12, 0.57)
CI=Confidence Interval
Note: If death dates were unknown, patients were censored at the last known date alive.

Figure 2. Kaplan-Meier Overall Survival Curve for ZYCUBO Late Treatment and External Control Late Treatment Cohorts with Menkes Disease

CuHis=copper histidinate; LT=late treatment; EC=external control

In the ZYCUBO-LT cohort, 11 (31.4%) patients survived >6 years, including 1 patient (2.9%) who survived >12 years. In the EC-LT cohort, no patients survived >6 years.

16 HOW SUPPLIED/STORAGE AND HANDLING

How Supplied

ZYCUBO (copper histidinate) for injection is supplied as a sterile, preservative-free, blue lyophilized powder or cake in a single-dose vial. Each vial contains 2.9 mg of copper histidinate (equivalent to 0.5 mg elemental copper). ZYCUBO is available as:

- One 2.9 mg single-dose vial in a carton: NDC 42358-329-01

Storage and Handling

Store ZYCUBO vials refrigerated at 2°C to 8°C (36°F to 46°F) in the original carton.

Store ZYCUBO reconstituted solution either refrigerated or at controlled room temperature [see Dosage and Administration (2.5)].

17 PATIENT COUNSELING INFORMATION

Advise the patient and/or caregiver to read the FDA-approved patient labeling (Instructions for Use).

Drug-Induced Kidney Injury, Liver Dysfunction, and Hematological Abnormalities

Advise the patient and/or caregiver of the potential for the patient to experience drug-induced kidney injury, liver dysfunction, and hematological abnormalities. [see Warnings and Precautions (5.1)].

Manufactured by:
Zydus Lifesciences Ltd.
Vadodara 391510
India

Manufactured for:
Sentynl Therapeutics, Inc.
Solana Beach, CA 92075

ZYCUBO is a registered trademark of Sentynl Therapeutics, Inc.

INSTRUCTIONS FOR USE

ZYCUBO® [zye kyoo boe]

(copper histidinate)

for injection, for subcutaneous use

This Instructions for Use contains information on how to prepare and inject ZYCUBO. Read this Instructions for Use before you prepare and inject a dose of ZYCUBO for the first time and each time you get a ZYCUBO refill. There may be new information. This information does not take the place of talking to your healthcare provider about your child's medical condition or their treatment.

ZYCUBO is for subcutaneous injection only (inject directly under the skin). Always follow the specific instructions given by your healthcare provider.

- If you have questions about preparing or injecting ZYCUBO, call SentynlCares | ZYCUBO Patient Support Services at 1-888-251-2800.

Important information you need to know before preparing and injecting ZYCUBO:

- Your healthcare provider should show you the right way to prepare and inject your child's prescribed dose of ZYCUBO before you do this for the first time.
- Your healthcare provider will prescribe the amount of ZYCUBO needed for each dose for your child. Confirm the amount of ZYCUBO needed at each visit with your child's healthcare provider.
- ZYCUBO comes as a powder or cake in a vial. Each vial of ZYCUBO must be mixed with 0.9% sodium chloride to mix (dissolve) the powder or cake before use.
- Do not mix ZYCUBO with anything other than 0.9% sodium chloride.
- Vials of ZYCUBO are for 1 time use only. Throw the vial away after use, even if there is medicine left in the vial. Do not save for later use. Throw away used vials in your household trash.
- If your child misses a dose of ZYCUBO, inject the dose as soon as possible. Inject the next scheduled dose at least 6 hours after you finish injecting the missed dose.
- Do not expose ZYCUBO to any heat source, such as a microwave or hot water.
- Do not share needles and syringes. See Step 13: “Throw away (dispose of) used needles and syringes.”

Storing ZYCUBO and other supplies:

Vials of ZYCUBO before mixing:

- Store ZYCUBO in the refrigerator between 36°F to 46°F (2°C to 8°C).
- Keep ZYCUBO vials in the original carton until you are ready to use it.

Vials of ZYCUBO after mixing:

- If you do not use the ZYCUBO solution right away after mixing, store the mixed ZYCUBO vial:
  - in the refrigerator between 36°F to 46°F (2°C to 8°C) and use within 24 hours. Throw away (discard) the mixed ZYCUBO vial if not used within 24 hours.
  - at room temperature between 68°F to 77°F (20°C to 25°C) and use within 4 hours. Throw away (discard) the mixed ZYCUBO vial if not used within 4 hours.
- Write the date and time you mixed ZYCUBO with 0.9% sodium chloride on the carton.
- Do not shake ZYCUBO after it has been mixed.

Other supplies:

- Store other supplies according to the manufacturer instructions (see Step 2: “Gather and check other supplies” for a list of supplies needed).

Keep ZYCUBO and all medicines out of the reach of children.

Preparing and injecting ZYCUBO

Step 1: Gather and check ZYCUBO vial for damage and expiration date

a) Remove the ZYCUBO carton from the refrigerator. Remove the ZYCUBO vial from the carton.
b) Check the ZYCUBO vial for damage and the expiration date.
  - Do not use the vial and contact the healthcare provider if the vial is damaged, expired or the flip-off cap on the vial is broken or missing.
c) Allow the ZYCUBO vial to sit at room temperature for about 30 minutes.

Step 2: Gather and check other supplies

- 1 vial of 0.9% sodium chloride
  - Check the expiration date on the vial.
  - Do not use the vial if the expiration date has passed.
  - Do not use the vial if the flip-off cap on the vial is broken or missing.
- One (1) sterile, 3 mL syringe with 1 inch needle (16 to 22 gauge) for preparing ZYCUBO
- One (1) sterile, 1 mL syringe with 1/2 inch needle (23 to 27 gauge) for injecting ZYCUBO.
  - Check the expiration dates of both sterile syringes with sterile needles.
  - Do not use if the expiration date has passed.
  - Do not use if the packaging is damaged.
- Alcohol wipes
- Gauze pads or Cotton ball
- 1 sharps disposal container (see Step 13: “Throw away (dispose of) used needles and syringes”)
- Gloves (if instructed by your healthcare provider)

Step 3: Wash your hands
If you have been told to wear gloves to prepare and inject ZYCUBO, put them on now.

Step 4: Prepare the vials

a) Remove the flip-off cap from the sodium chloride vial and ZYCUBO vial.
b) Throw away (discard) the vial caps in the trash.
c) Clean the rubber stopper of each vial with an alcohol wipe and allow to air dry.
  - Do not blow on the stopper to dry it faster.

Note: If you touch the rubber stopper, clean it again with a new alcohol wipe.

Step 5: Prepare the syringe used for withdrawing sodium chloride

a) Remove a 3 mL syringe with needle from the plastic packaging.
b) Pull the needle cover straight off and throw it away in the trash.
  - Do not touch the needle or let the needle touch any surface.

Step 6: Withdraw 1 mL of sodium chloride into syringe

a) Hold the syringe barrel with one hand. With your other hand, draw air into the syringe by pulling back on the plunger rod until the top of the plunger lines up with the 1 mL mark on the syringe.
b) Hold the sodium chloride vial on a clean, flat work surface and insert the needle into the center of the sodium chloride vial stopper.
  Note: If you remove the needle at any point, clean the rubber stopper with a new alcohol wipe before reinserting the needle.
c) Turn the vial upside down.
d) Slowly push up on the plunger rod to push all the air from the syringe into the vial.
e) Make sure the tip of the needle is in the sodium chloride solution. Slowly pull down on the plunger rod of the syringe until the top of the plunger reaches the 1 mL mark on the syringe.
f) Gently tap the syringe barrel to remove as many air bubbles as possible. It is acceptable if some air bubbles remain in the syringe after you tap the syringe.
  - Push the plunger rod up to remove as many large air bubbles as you can.
g) Check to make sure that 1 mL of sodium chloride has been withdrawn into the syringe. If the amount is less than 1 mL, repeat Steps 6e and 6f until you have 1 mL of sodium chloride.
h) Remove the needle and syringe from the sodium chloride vial. Be careful not to move the plunger.

Step 7: Mix ZYCUBO until dissolved

a) Hold the ZYCUBO vial on a clean, flat work surface.
b) Insert the syringe with 1 mL of sodium chloride into the center of the ZYCUBO vial stopper.
c) Tilt the vial so that the tip of the needle is pointing toward the inside wall of the vial.
  - With your thumb, slowly push the plunger rod down all the way. The liquid should go down the inside wall of the vial.
d) Carefully remove the needle from the vial. Throw away (dispose of) the used needle and syringe in your sharps disposal container right away.
  - Do not try to recap the needle.See Step 13: “Throw away (dispose of) used needles and syringes.”
e) Gently swirl the vial continuously until the powder is completely dissolved. Do not shake the vial.

Step 8: Check solution
Check that the ZYCUBO solution is a blue color.

- Do not use if the mixed solution is not a blue color, is cloudy, or contains particles. Ask your pharmacist for a replacement vial.

Step 9: Determine the injection time
After mixing, inject the ZYCUBO solution right away or inject the ZYCUBO solution:

- within 24 hours if stored in the refrigerator. Throw away (discard) the mixed ZYCUBO vial if not used within 24 hours.
  - If you store the mixed ZYCUBO vial in the refrigerator, remove the vial from the refrigerator and allow it to sit at room temperature for about 30 minutes.
- within 4 hours if stored at room temperature. Throw away (discard) the mixed ZYCUBO vial if not used within 4 hours.
- If you do not inject the ZYCUBO solution right away:
  - Wash your hands well with soap and water.
  - Wipe the rubber stopper of the mixed ZYCUBO vial with a new alcohol wipe and allow to air dry.
    - Do not blow on the rubber stopper to dry faster.

Step 10: Prepare a syringe with the prescribed dose of ZYCUBO

a) Remove a 1 mL syringe with needle from the plastic packaging.
b) Pull the needle cover straight off and throw it away in the trash.
  - Do not touch the needle or let the needle touch any surface.
c) Hold the mixed ZYCUBO vial on a clean, flat work surface and insert the needle into the center of the ZYCUBO vial stopper.
  Note: If you remove the needle at any point, clean the rubber stopper with a new alcohol wipe before reinserting the needle.
d) Turn the vial upside down.
e) Move the needle so that the tip is in the ZYCUBO solution.
f) Slowly pull back on the plunger rod to fill the syringe with 0.5 mL of ZYCUBO solution. The top of the plunger should line up with the 0.5 mL mark on the syringe.
g) Gently tap the syringe barrel to remove as many air bubbles as possible. It is acceptable if some air bubbles remain in the syringe after you tap the syringe.
  - Push the plunger rod up to remove as many large air bubbles as you can.
h) Check to make sure that 0.5 mL of ZYCUBO solution has been withdrawn into the syringe. If the amount is less than 0.5 mL, repeat Steps 10f and 10g until you have 0.5 mL of ZYCUBO solution.
i) Remove the needle and syringe from the ZYCUBO vial.
j) Throw away the used ZYCUBO vial in your household trash after use, even if there is medicine left in the vial.

Step 11: Prepare the injection site
ZYCUBO is injected under the skin (subcutaneously).

a) Choose one (1) of the following injection sites:
  - stomach area (abdominal area), 2 inches from belly button,
  - buttocks, or
  - outer area of the upper arm or thigh.

- Change (rotate) the injection site with each injection to reduce your risk of skin problems.
- Do not give injections into areas where the skin is scarred, tender, bruised, red or hard.

b) Clean the injection site with a new alcohol wipe.
c) Let the injection site air dry.
  - Do not touch, wipe, fan, or blow on it.

Step 12: Inject ZYCUBO

a) Pinch the skin around the clean injection site with one hand. With the other hand, hold the syringe and fully insert the needle into the skin at a 45-degree angle. Do not press the plunger rod until you are ready to inject.
b) Push the plunger rod all the way down to inject all of the ZYCUBO solution.
c) Remove the needle from the injection site at the same 45-degree angle it was inserted.
  - If you see any blood, lightly press a cotton ball or gauze at the injection site. Apply an adhesive bandage if necessary. Do not rub the injection site.
  - If the injection site becomes red or sore, call your healthcare provider right away.

Step 13: Throw away (dispose of) used needles and syringes

- Put your used needles and syringes in an FDA-cleared sharps disposal container right away after use. Do not throw away (dispose of) needles and syringes in your household trash.
- If you do not have an FDA-cleared sharps disposal container, you may use a household container that is:
  - made of heavy-duty plastic,
  - can be closed with a tight-fitting, puncture-resistant lid, without sharps being able to come out,
  - upright and stable during use,
  - leak-resistant, and
  - properly labeled to warn of hazardous waste inside the container.
- When your sharps disposal container is almost full, you will need to follow your community guidelines for the right way to dispose of your sharps disposal container. There may be state or local laws about how you should throw away used needles and syringes. For more information about safe sharps disposal, and for specific information about sharps disposal in the state that you live in, go to the FDA's website at: https://www.fda.gov/safesharpsdisposal.
- Do not dispose of your used sharps disposal container in your household trash unless your community guidelines permit this. Do not recycle your used sharps disposal container.
- Keep the sharps disposal container out of the reach of children.

If you have questions about preparing or injecting ZYCUBO, call SentynlCares | ZYCUBO Patient Support Services at 1-888-251-2800.
Manufactured by: Zydus Lifesciences Ltd., Vadodara – 391510, India
Manufactured for: Sentynl Therapeutics, Inc., Solana Beach, CA 92075
This Instructions for Use has been approved by the U.S. Food and Drug Administration.
Issued: 1/2026

Principal Display Panel - 2.9 mg Carton Label

NDC 42358-329-01

Zycubo ®
(copper histidinate) for injection

2.9 mg/vial

For subcutaneous injection

One Single-Dose vial

Discard unused portion after each single use.
Do not administer more than one dose from the vial.

Rx only

Principal Display Panel - 2.9 mg Vial Label

NDC 42358-329-01 Rx only

Zycubo ®
(copper histidinate) for injection

2.9 mg/vial

For subcutaneous injection

One Single-Dose vial

Discard unused portion after each single use.
Do not administer more than one dose from the vial.